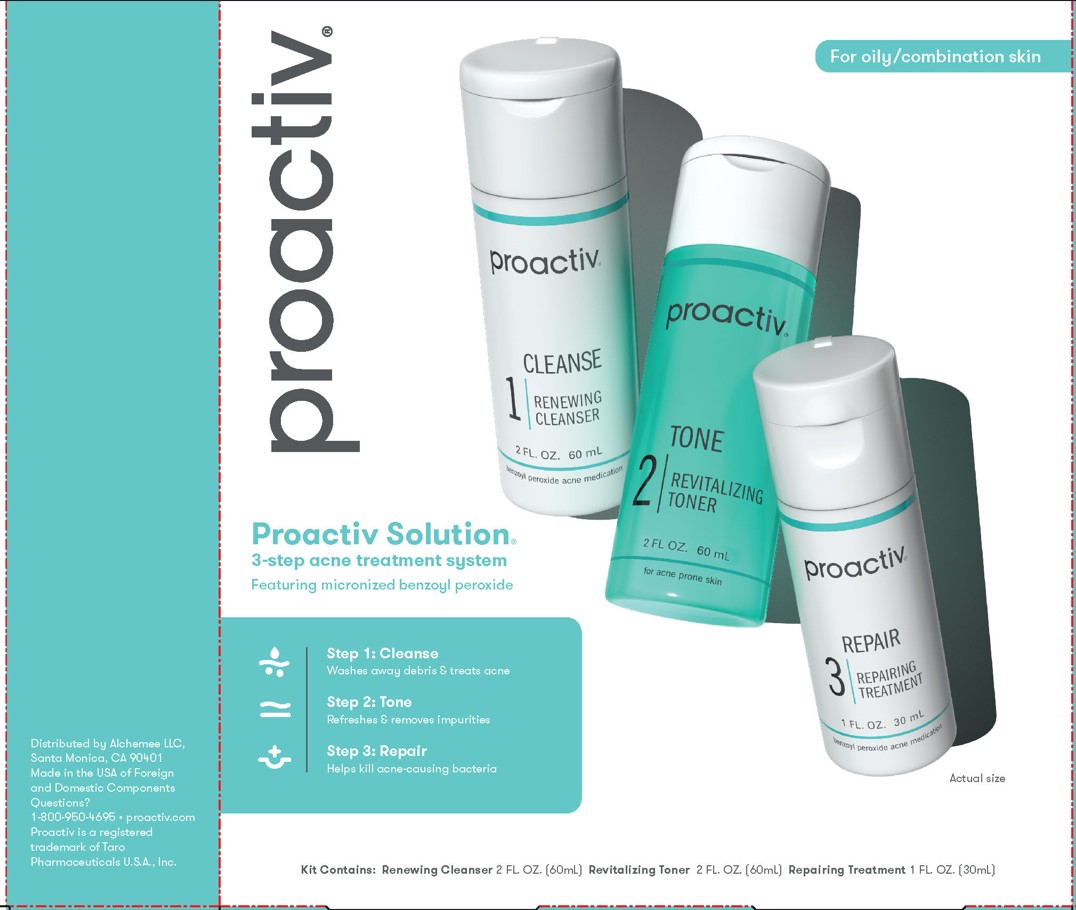 DRUG LABEL: Proactiv Solution Kit
NDC: 11410-215 | Form: KIT | Route: TOPICAL
Manufacturer: Alchemee, LLC
Category: otc | Type: HUMAN OTC DRUG LABEL
Date: 20260107

ACTIVE INGREDIENTS: BENZOYL PEROXIDE 2.5 g/100 mL; BENZOYL PEROXIDE 2.5 mg/100 mL
INACTIVE INGREDIENTS: WATER; MAGNESIUM ALUMINUM SILICATE; DIMETHYL ISOSORBIDE; TRIDECYL STEARATE; CHAMAEMELUM NOBILE; SODIUM PYRROLIDONE CARBOXYLATE; PARAFFIN; TRIDECYL TRIMELLITATE; PHENOXYETHANOL; GLYCERYL MONOSTEARATE; SORBITOL; TRISODIUM SULFOSUCCINATE; XANTHAN GUM; PROPYLPARABEN; PEG-100 STEARATE; NEOPENTYL GLYCOL DICAPRYLATE/DICAPRATE; CETYL ESTERS WAX; PEG-12 DIMETHICONE (300 CST); HYALURONATE SODIUM; PROPYLENE GLYCOL; METHYLPARABEN; PROPYLENE GLYCOL; WATER; CETOSTEARYL ALCOHOL; CYCLOMETHICONE 5; DIMETHICONE; PEG-100 STEARATE; PANTHENOL; PROPYLPARABEN; DIETHYLENE GLYCOL MONOETHYL ETHER; ALLANTOIN; POLYOXYL 20 CETOSTEARYL ETHER; METHYLPARABEN; GLYCERYL MONOSTEARATE; SODIUM HYDROXIDE; XANTHAN GUM; DIAZOLIDINYL UREA; CARBOMER HOMOPOLYMER, UNSPECIFIED TYPE

Proactiv Solution 30 Day Kit

Renewing Cleanser - Drug Facts

Drug Facts

Repairing Treatment - Drug Facts

Drug Facts

Renewing Cleanser- Active ingredient

Benzoyl peroxide 2.5%

Repairing Treatment - Active Ingredient

Benzoyl peroxide 2.5%

Renewing Cleanser - Purpose

Acne treatment

Repairing Treatment - Purpose

Acne treatment

Renewing Cleanser - Use

for the management of acne

Repairing Treatment - Use

for the management of acne

Renewing Cleanser - Warnings

For external use only

Renewing Cleanser - When using this product

- skin irritation and dryness is more likely to occur if you use another topical acne medication at the same time. If irritation occurs, only use one topical acne medication at a time.
- avoid unnecessary sun exposure and use a sunscreen.
- avoid contact with the eyes, lips, and mouth.
- avoid contact with hair and dyed fabrics, which may be bleached by this product.
- skin irritation may occur, characterized by redness, burning, itching, peeling, or possibly swelling. Irritation may be reduced by using the product less frequently or in a lower concentration.

Do not useif you

- have very sensitive skin
- are sensitive to benzoyl peroxide

Stop use and ask a doctor if

- irritation becomes severe.

Keep out of reach of children.If swallowed, get medical help or contact a Poison Control Center right away.

Repairing Treatment - Warnings

For external use only

Renewing Cleanser - When using this product

skin irritation and dryness is more likely to occur if you use another topical acne medication at the same time. If irritation occurs, only use one topical acne medication at a time.
avoid unnecessary sun exposure and use a sunscreen.
avoid contact with eyes, lips and mouth.
avoid contact with hair and dyed fabrics, which may be bleached by this product.

skin irritation may occur, characterized by redness, burning, itching, peeling or possibly swelling. Irritation may be reduced by using the product less frequently or in a lower concentration.

Repairing Treatment - When using this product

skin irritation and dryness is more likely to occur if you use another topical acne medication at the same time. If irritation occurs, only use one topical acne medication at a time.
avoid unnecessary sun exposure and use a sunscreen.
avoid contact with eyes, lips and mouth.
avoid contact with hair and dyed fabrics, which may be bleached by this product.

skin irritation may occur, characterized by redness, burning, itching, peeling or possibly swelling. Irritation may be reduced by using the product less frequently or in a lower concentration.

Renewing Cleanser - Do not use if you

have very sensitive skin.

Repairing Treatment - Do not use if you

have very sensitive skin.

are sensitive to benzoyl peroxide.

Renewing Cleanser - Stop use and ask a doctor if

Irritation becomes Severe

Repairing Treatment - Stop use and ask a doctor if

irritation becomes severe.

Renewing Cleanser - Keep out of reach of children

If swallowed, call a Poison Control Center or get medical help right away.

Repairing Treatment - Keep out of reach of children

If swallowed, call a Poison Control Center or get medical help right away.

Repairing Treatment - Keep out of reach of children

If swallowed, call a Poison Control Center or get medical help right away.

Renewing Cleanser - Directions

- Sensitivity Test for a New User . Apply product sparingly to one or two small affected areas during the first 3 days. If no discomfort occurs, follow the directions stated below.
- cover the entire affected area with a thin layer and rinse thoroughlyone to three times daily.
- because excessive drying of the skin may occur, start with one application daily, then gradually increase to two or three times daily if needed or as directed by a doctor.
- if bothersome dryness or peeling occurs, reduce application to once a day or every other day.
- if going outside, apply sunscreen after using this product. If irritation or sensitivity develops, stop use of both products and ask a doctor.

Repairing Treatment - Directions

Sensitivity Test for a New User. Apply product sparingly to one or two small affected areas during the first 3 days. If no discomfort occurs, follow the directions stated below.
clear the skin thoroughly before applying this product.
cover the entire affected area with a thin layer one to three times daily.
because excessive drying of the skin may occur, start with one application daily, then gradually increase to two or three times daily if needed or as directed by a doctor.
if bothersome dryness or peeling occurs, reduce application to once a day or every other day.

if going outside, apply sunscreen after using this product. If irritation or sensitivity develops, stop use of both products and ask a doctor.

Repairing Treatment - other information

Store at 20oC – 25oC (68o – 77oF).

Renewing Cleanser - Other information

Store at 20oC – 25oC (68o – 77oF).

Repairing Treatment - Other Informations

Store at 20oC – 25oC (68o – 77oF).

Renewing Cleanser - Inactive ingredients

water, magnesium aluminum silicate, glyceryl stearate, PEG-100 stearate, sorbitol, dimethyl isosorbide, disodium PEG-12 dimethicone sulfosuccinate, tridecyl stearate, neopentyl glycol dicaprylate/dicaprate, paraffin, cetyl esters, tridecyl trimellitate, trisodium sulfosuccinate, PEG-12 dimethicone, xanthan gum, imidazolidinyl urea, fragrance, methylparaben, sodium sulfate, propylparaben, sodium PCA, propylene glycol, anthemis nobilis flower extract, phenoxyethanol, sodium hyaluronate

Repairing Treatment - Inactive Ingredient

water, ethoxydiglycol, cyclopentasiloxane, propylene glycol, cetearyl alcohol, glyceryl stearate, PEG-100 stearate, dimethicone, ceteareth-20, diazolidinyl urea, carbomer, fragrance, methylparaben, xanthan gum, panthenol, allantoin, sodium hydroxide, propylparaben.

Questions or comments?

1-800-950-4695

Distributed by Alchemee LLC
Santa Monica, CA 90401
Made in the USA of Foreign
and Domestic Components
Questions? 1-800-950-4695 • proactiv.com
Proactiv is a registered trademark
of Taro Pharmaceuticals U.S.A., Inc.

PRINCIPAL DISPLAY PANEL - Proactiv Solution Kit

proactiv®

Proactiv Solution

3-step acne treatment system

Featuring micronized benzoyl peroxide

Step 1: Cleanse

Washes away debris & treats acne

Step 2: Tone

Refreshes & removes impurities

Step 3: Repair

Helps Kill acne-causing bacteria

Kits Contains: RENEWING CLEANSER 2 FL. OZ. (60 mL) Revitalizing Toner 2 FL. OZ. (60 mL) Repairing Treatment 1 FL. OZ. (30mL)